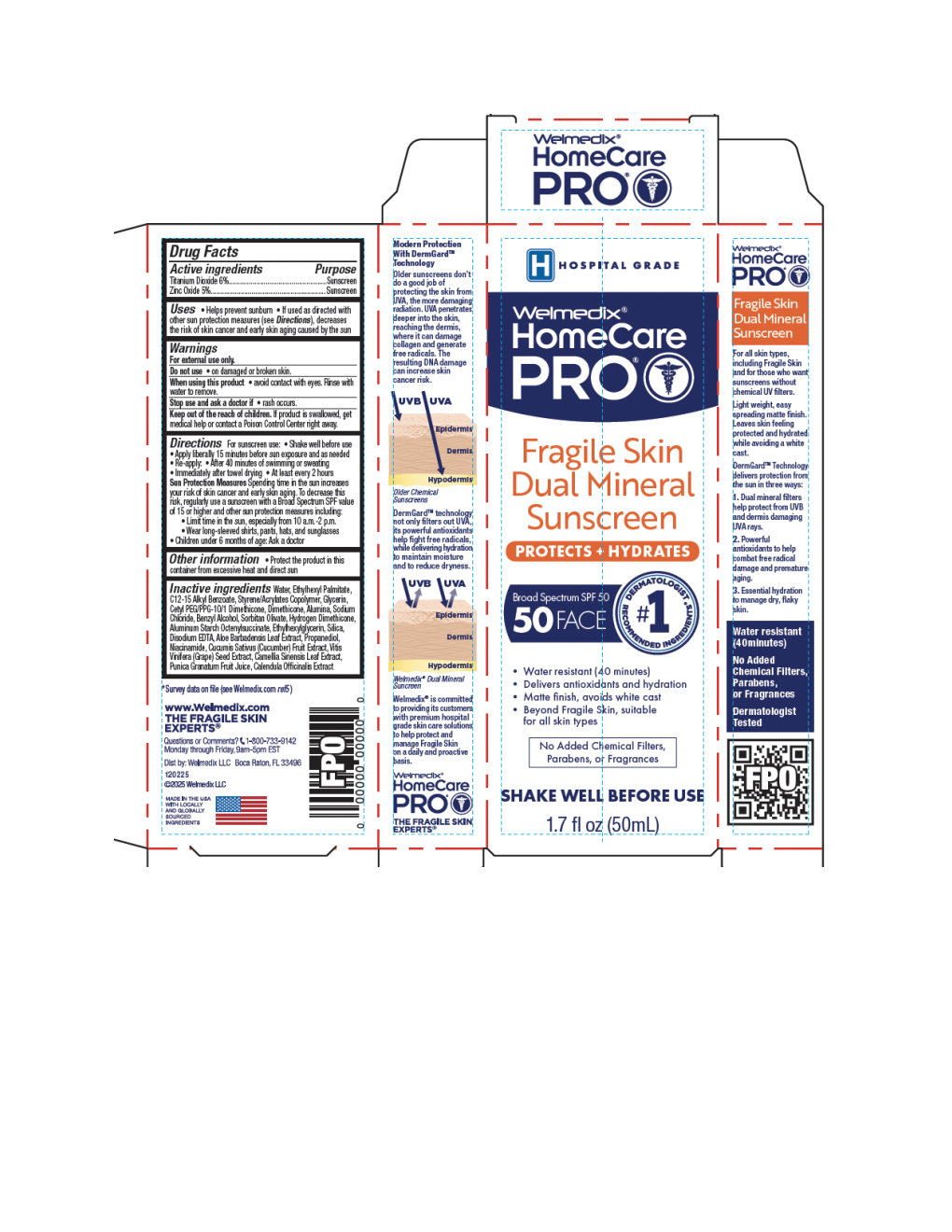 DRUG LABEL: Welmedix HomeCare PRO Fragile Skin Dual Mineral Sunscreen
NDC: 24330-415 | Form: LOTION
Manufacturer: Welmedix LLC
Category: otc | Type: HUMAN OTC DRUG LABEL
Date: 20260120

ACTIVE INGREDIENTS: TITANIUM DIOXIDE 60 mg/1 mL; ZINC OXIDE 50 mg/1 mL
INACTIVE INGREDIENTS: ALOE BARBADENSIS LEAF; MAGNESIUM DISODIUM EDTA; SILICA DIMETHYL SILYLATE; WATER; ETHYLHEXYL PALMITATE; C12-15 ALKYL BENZOATE; STYRENE/ACRYLAMIDE COPOLYMER (MW 500000); GLYCERIN; CETYL PEG/PPG-10/1 DIMETHICONE (HLB 2); DIMETHICONE 100; ALUMINA; SODIUM CHLORIDE; BENZYL ALCOHOL; SORBITAN OLIVATE; HYDROGEN DIMETHICONE (13 CST); NIACINAMIDE; CUCUMIS SATIVUS (CUCUMBER) FRUIT; ETHYLHEXYLGLYCERIN; ALUMINUM STARCH OCTENYLSUCCINATE; PUNICA GRANATUM FRUIT JUICE; CALENDULA OFFICINALIS FLOWER; VITIS VINIFERA (GRAPE) SEED OIL; CAMELLIA SINENSIS LEAF; PROPANEDIOL

Welmedix®HomeCare PRO Fragile Skin Dual Mineral Sunscreen

Active ingredients

Titanium Dioxide 6%
Zinc Oxide 5%

Purpose

Sunscreen

Uses

- Helps prevent sunburn

Warnings

For external use only

When using this product, avoid contact with eyes. Rinse with water to remove.

Stop use and ask doctor if

- rash occurs

Keep out of reach of children.

If product is swallowed, get medical help or contact a Poison Control Center right away.

Directions:

- Shake well before use
- Apply liberally 15 minutes before sun exposure and as needed
- Re-apply:
  - After 40 minutes of swimming or sweating
  - Immediately after towel drying
  - At least every 2 hours

Other Information:

Protect the product from excessive heat and direct sun.

Inactive ingredients

Water, Ethylhexyl Palmitate, C12-15 Alkyl Benzoate, Styrene/Acrylates Copolymer, Glycerin, Cetyl PEG/PPG-10/1 Dimethicone, Dimethicone, Alumina, Sodium Chloride, Benzyl Alcohol, Sorbitan Olivate, Hydrogen Dimethicone, Aluminum Starch Octenylsuccinate, Ethylhexylglycerin, Silica, Disodium EDTA, Aloe Barbadensis Leaf Extract, Propanediol, Niacinamide, Cucumis Sativus (Cucumber) Fruit Extract, Vitis Vinifera (Grape) Seed Extract, Camellia Sinensis Leaf Extract, Punica Granatum Fruit Juice, Calendula Officinalis Extract

Principal Display Panel Tube

Welmedix®HomeCare PRO

Fragile Skin Dual Mineral Sunscreen

Protects + Hydrates

Net Wt 1.7 fl oz (50mL)